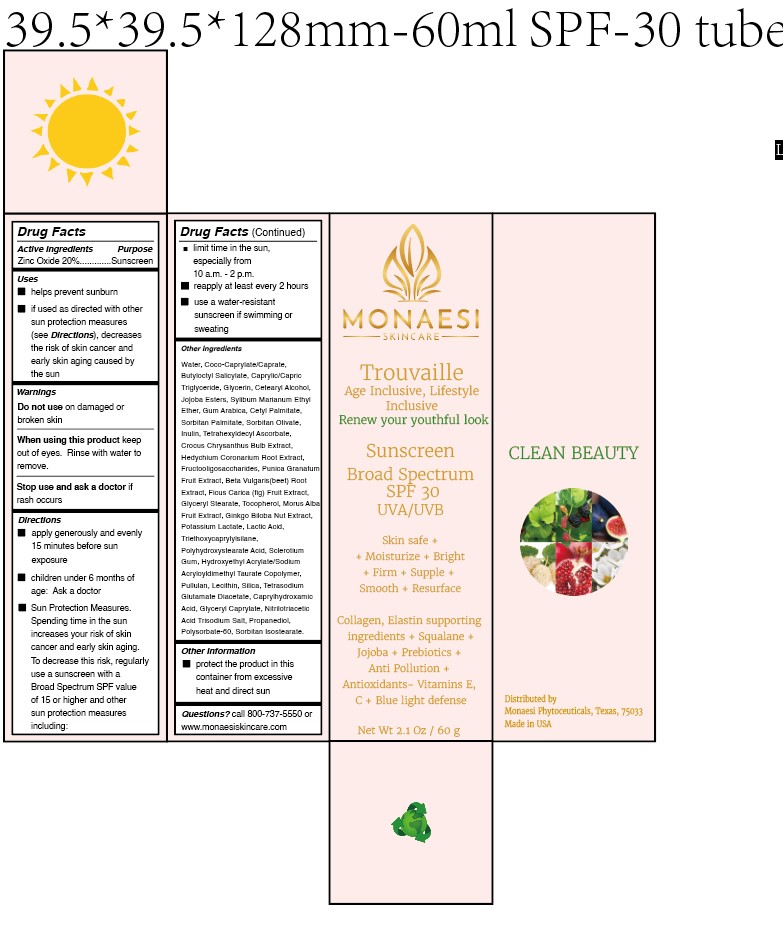 DRUG LABEL: Trouvaille Sunscreen Broad Spectrum SPF 30 UVA/UVB
NDC: 82285-120 | Form: CREAM
Manufacturer: Monaesi Phytoceuticals
Category: otc | Type: HUMAN OTC DRUG LABEL
Date: 20220214

ACTIVE INGREDIENTS: ZINC OXIDE 20 mg/100 mg
INACTIVE INGREDIENTS: COCO-CAPRYLATE/CAPRATE 7 mg/100 mg

I am trying to list sunscreen.

Active Ingredient(s)

Zinc oxide

Purpose

sunscreen

Use

helps prevent sunburn”

Warnings

Do not use on damaged or broken skin”
“When using this product keep out of eyes. Rinse with water to remove.”
“Stop use and ask a doctor if rash occurs”

For sunscreen drug products that do not pass the Broad Spectrum Test or that have SPF values less than 15, the first statement under Warnings must be:
“Skin Cancer/Skin Aging Alert: Spending time in the sun increases your risk of skin cancer and early skin aging. This product has been shown only to help prevent sunburn, not skin cancer or early skin aging.”

“Do not use on damaged or broken skin”

When using this product keep out of eyes. Rinse with water to remove

“Stop use and ask a doctor if rash occurs

Other information

“protect the product in this container from excessive heat and direct sun

Inactive ingredients

Water, Coco-Caprylate/Caprate, Butyloctyl Salicylate, Caprylic/Capric Triglyceride, Glycerin, Cetearyl Alcohol, Jojoba Esters, Sylibum Marianum Ethyl Ether, Gum Arabica, Cetyl Palmitate, Sorbitan Palmitate, Sorbitan Olivate, Inulin, Tetrahexyldecyl Ascorbate, Crocus Chrysanthus Bulb Extract, Hedychium Coronarium Root Extract, Fructooligosaccharides, Punica Granatum Fruit Extract, Beta Vulgaris(beet) Root Extract, Ficus Carica (fig) Fruit Extract, Glyceryl Stearate, Tocopherol, Morus Alba Fruit Extracf, Ginkgo Biloba Nut Extract, Potassium Lactate, Lactic Acid, Triethoxycaprylylsilane, Polyhydroxystearate Acid, Sclerotium Gum, Hydroxyethyl Acrylate/Sodium Acryloyldimethyl Taurate Copolymer, Pullulan, Lecithin, Silica, Tetrasodium Glutamate Diacetate, Caprylhydroxamic Acid, Glyceryl Caprylate, Nitrilotriacetic Acid Trisodium Salt, Propanediol, Polysorbate-60, Sorbitan Isostearate

Package Label - Principal Display Panel

NDC: 82285-020-01

Please see the attached image

Sunscreen

Broadspectrum

SPF 30

UVA/UVB